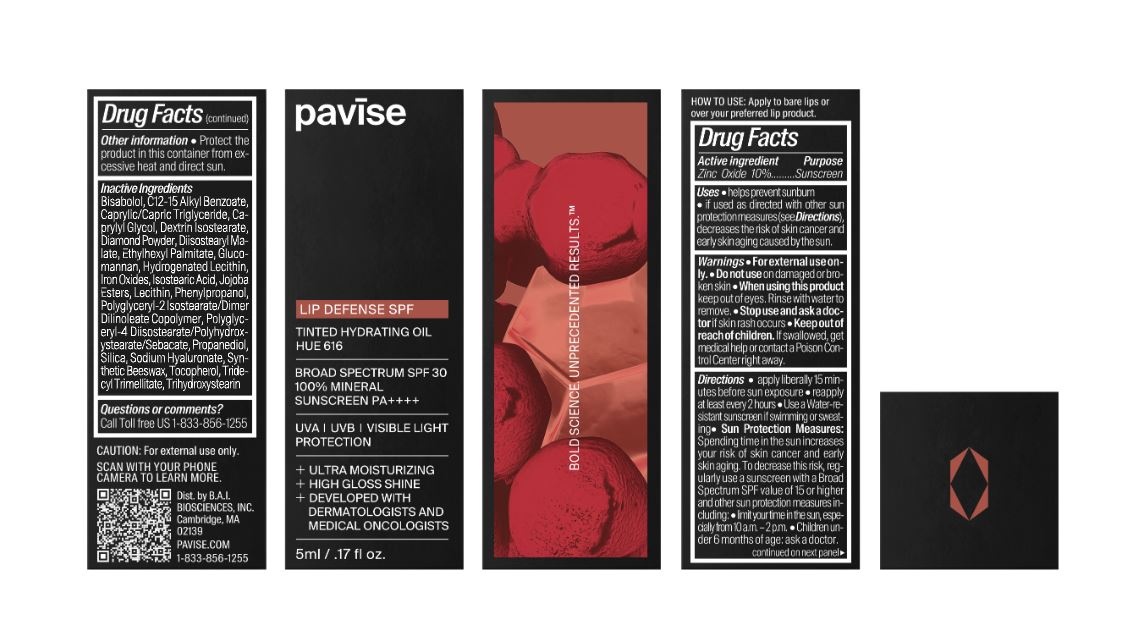 DRUG LABEL: pavise Lip Defense tinted hydrating oil (hue 616)
NDC: 83100-1762 | Form: LOTION
Manufacturer: B.A.I. Biosciences INC.
Category: otc | Type: HUMAN OTC DRUG LABEL
Date: 20251009

ACTIVE INGREDIENTS: ZINC OXIDE 100 mg/1 mL
INACTIVE INGREDIENTS: FERRIC OXIDE RED; HYDROLYZED JOJOBA ESTERS (ACID FORM); DIAMOND; FERRIC OXIDE YELLOW; ISOSTEARIC ACID; SILICON DIOXIDE; POLYGLYCERYL-4 DIISOSTEARATE/POLYHYDROXYSTEARATE/SEBACATE; PHENYLPROPANOL; FERROSOFERRIC OXIDE; TOCOPHEROL; ETHYLHEXYL PALMITATE; DIISOSTEARYL MALATE; TRIDECYL TRIMELLITATE; .ALPHA.-BISABOLOL, (+)-; PROPANEDIOL; CAPRYLYL GLYCOL; LECITHIN, SOYBEAN; ALKYL (C12-15) BENZOATE; TRIHYDROXYSTEARIN; POLYGLYCERYL-2 ISOSTEARATE

pavise Lip Defense tinted hydrating oil (hue 616)